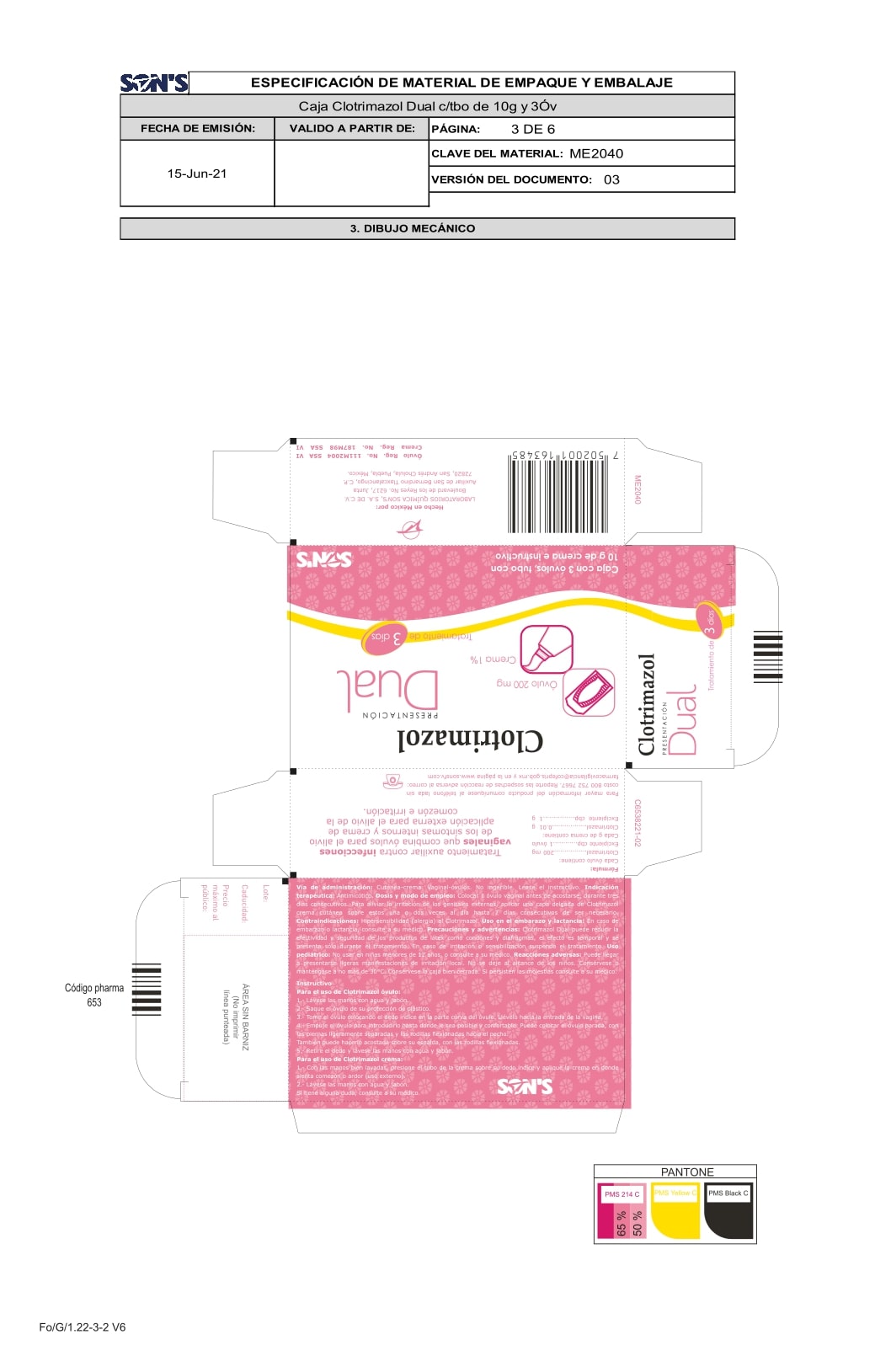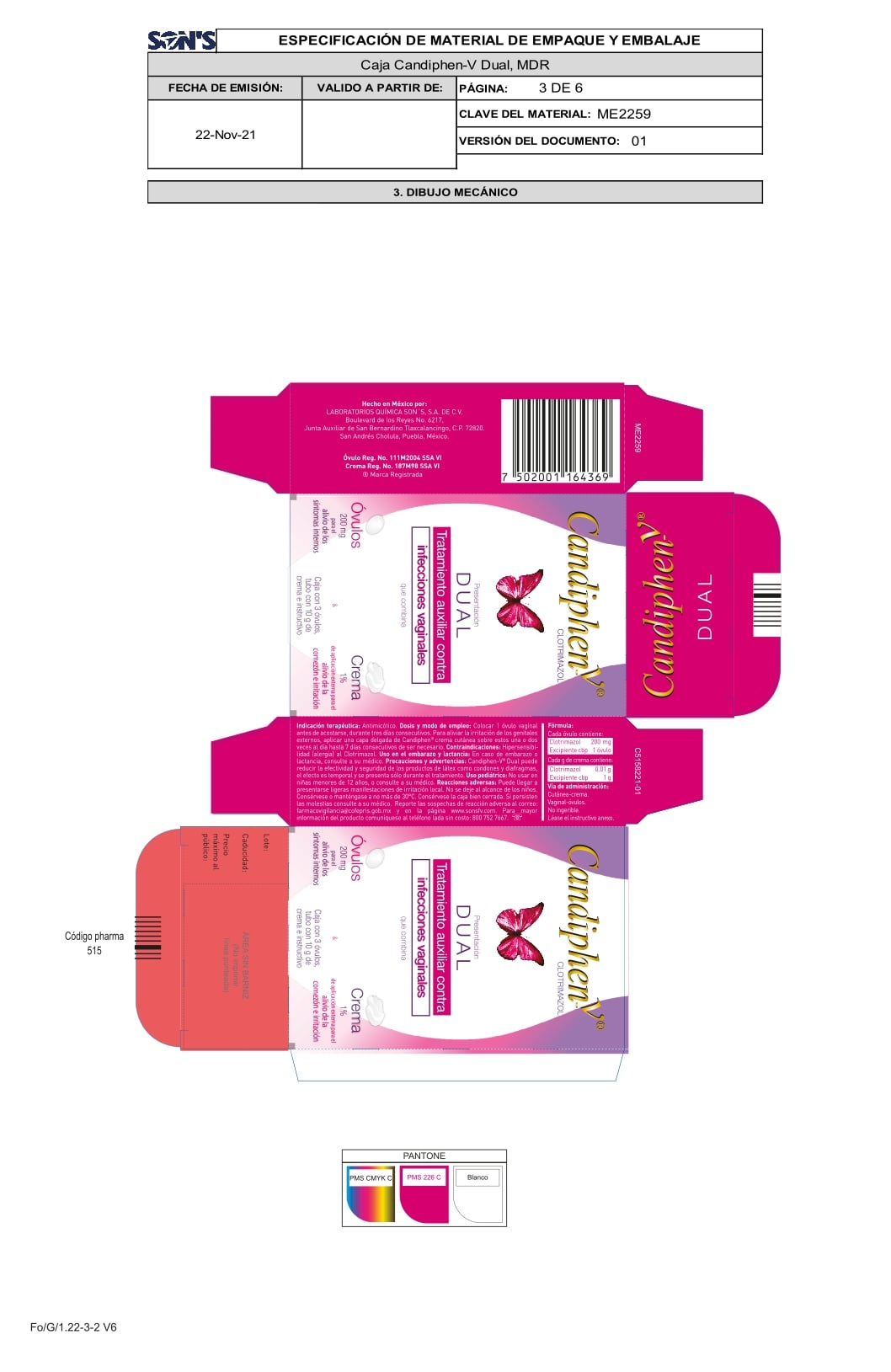 DRUG LABEL: CLOTRIMAZOL
NDC: 73519-003 | Form: CREAM
Manufacturer: Laboratorios Química Son's, S.A. de C.V.
Category: otc | Type: HUMAN OTC DRUG LABEL
Date: 20220111

ACTIVE INGREDIENTS: CLOTRIMAZOLE 0.2 g/1 g
INACTIVE INGREDIENTS: PEG-20 SORBITAN STEARATE 0.2 g/1 g; POLYSORBATE 80 0.1 g/1 g; SODIUM BISULFITE 0.2 g/1 g; METHYLPARABEN 0.0167 g/1 g; ISOPROPYL MYRISTATE 1 g/1 g; POLYSORBATE 60 0.15 g/1 g; PEG-25 PROPYLENE GLYCOL STEARATE 0.2 g/1 g; WATER 1 g/1 g; STEARYL ALCOHOL 0.75 g/1 g; CETYL ALCOHOL 0.2 g/1 g

CLOTRIMAZOL